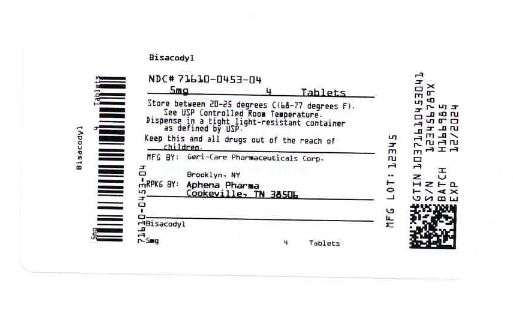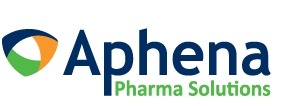 DRUG LABEL: stimulant laxative enteric coated
NDC: 71610-453 | Form: TABLET
Manufacturer: Aphena Pharma Solutions - Tennessee, LLC
Category: otc | Type: HUMAN OTC DRUG LABEL
Date: 20250109

ACTIVE INGREDIENTS: BISACODYL 5 mg/1 1
INACTIVE INGREDIENTS: ACACIA; AMMONIA; CALCIUM CARBONATE; CARNAUBA WAX; STARCH, CORN; D&C YELLOW NO. 10; FD&C YELLOW NO. 6; HYPROMELLOSES; FERROSOFERRIC OXIDE; LACTOSE MONOHYDRATE; MAGNESIUM STEARATE; METHYLPARABEN; POLYDEXTROSE; POLYETHYLENE GLYCOL, UNSPECIFIED; POLYVINYL ACETATE PHTHALATE; PROPYLPARABEN; PROPYLENE GLYCOL; POVIDONE; SHELLAC; DIMETHICONE; SILICON DIOXIDE; SODIUM ALGINATE; SODIUM BENZOATE; SODIUM BICARBONATE; STEARIC ACID; SUCROSE; TALC; TITANIUM DIOXIDE; TRIACETIN; TRIETHYL CITRATE

441

Active ingredient (in each tablet)

Bisacodyl 5 mg

Purpose

Stimulant Laxative

Uses

- relieves occasional constipation and irregularity

- generally produces a bowel movement in 6 to 12 hours

Warnings

Do not use
• for more than one week unless directed by a doctor
• if you cannot swallow without chewing
• within 1 hour after taking an antacid or milk

Ask a doctor before use if you have
• abdominal pain
• nausea
• vomiting
• a sudden change in bowel habits that lasts longer than 2 weeks

When using this product• abdominal discomfort, faintness, or cramps may occur

Stop use and ask a doctor
• if you have no bowel movement within 12 hours
• if you have rectal bleeding
• these could be signs of a serious condition

If pregnant or breast-feeding,ask a health professional before use.

Keep out of reach of children.In case of overdose, get medical help or contact a Poison Control Center right away.

Directions

• do not take more than directed
• swallow whole, do not chew or crush
• take recommended dose in a single daily dose
• take with water
• adults and children 12 years and older: take 1-3 (usually 2) tablets daily
• children 12 and under: ask a doctor

Other information

• store at room temperature
• avoid excessive humidity
• Tamper Evident: Do not use if imprinted seal under cap is missing or broken
• package not child resistant
• for institutional use only

Inactive ingredients

Acacia, Ammonium Hydroxide, Calcium Carbonate, Corn Starch, D and C Yellow NO. 10 Lake, FD and C Yellow NO. 6 Lake, Hypromellose, Iron Oxide Black, Lactose, Magnesium Stearate, Methylparaben, PEG, Polydextrose, Polyvinyl Acetate Phthalate, Propylparaben, Propylene Glycol, Povidone, Shellac, Simethicone, Silica, Sodium Alginate, Sodium Benzoate, Sodium Bicarbonate, Stearic Acid, Sucrose, Talc, Titanium Dioxide, Triacetin, Triethyl Citrate, Wax. May also contain: Calcium Sulfate, Gelatin, Sodium Starch Glycolate.

Repackaging Information

Please reference the How Suppliedsection listed above for a description of individual tablets. This drug product has been received by Aphena Pharma - TN in a manufacturer or distributor packaged configuration and repackaged in full compliance with all applicable cGMP regulations. The package configurations available from Aphena are listed below:

Count | 5 mg
2 | 71610-453-02
4 | 71610-453-04
20 | 71610-453-20

Store between 20°-25°C (68°-77°F). See USP Controlled Room Temperature. Dispense in a tight light-resistant container as defined by USP. Keep this and all drugs out of the reach of children.

Repackaged by:
Cookeville, TN 38506
20200805JH

PRINCIPAL DISPLAY PANEL - 5 mg

NDC 71610-453 - Bisacodyl 5 mg Tablets